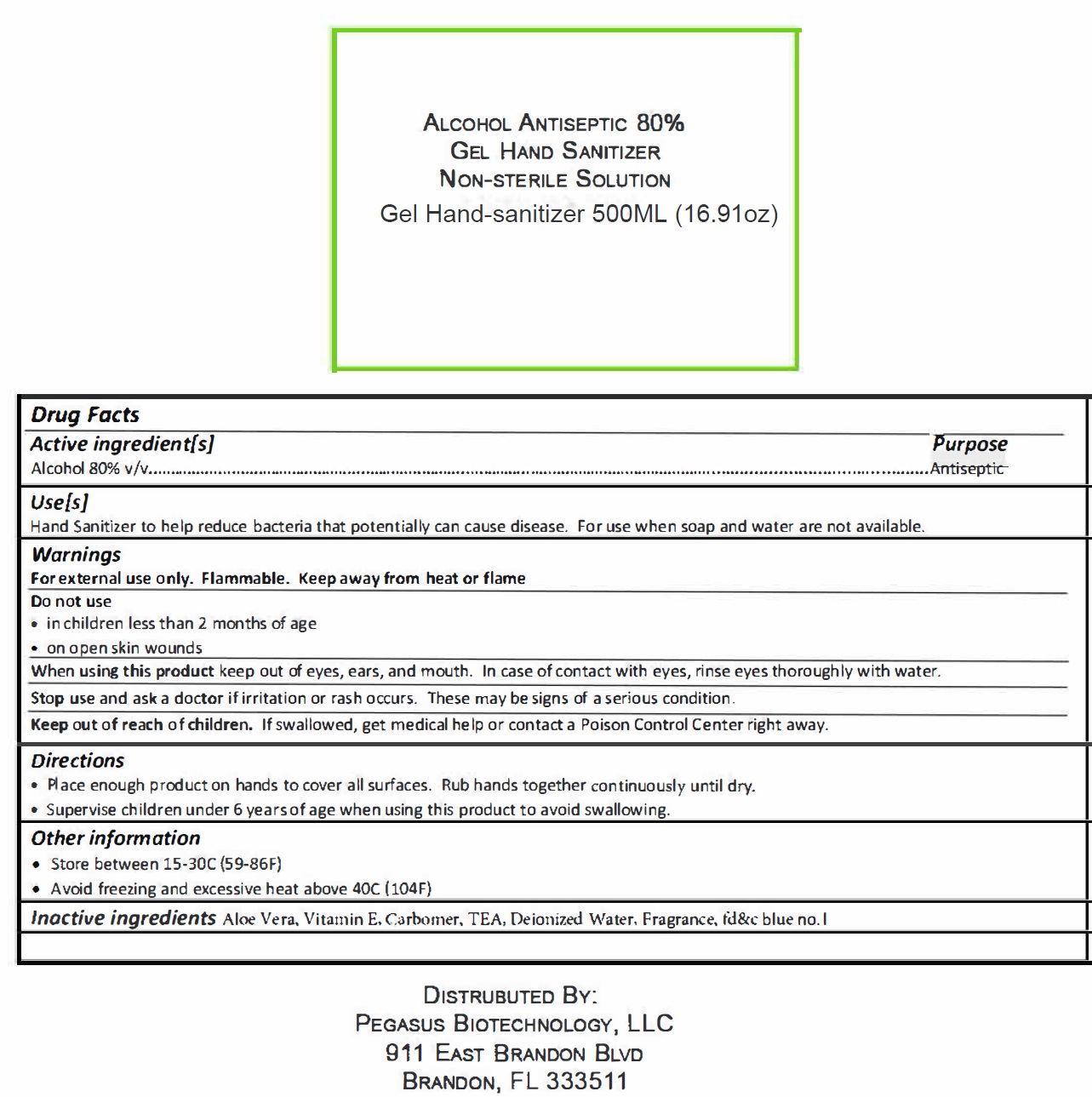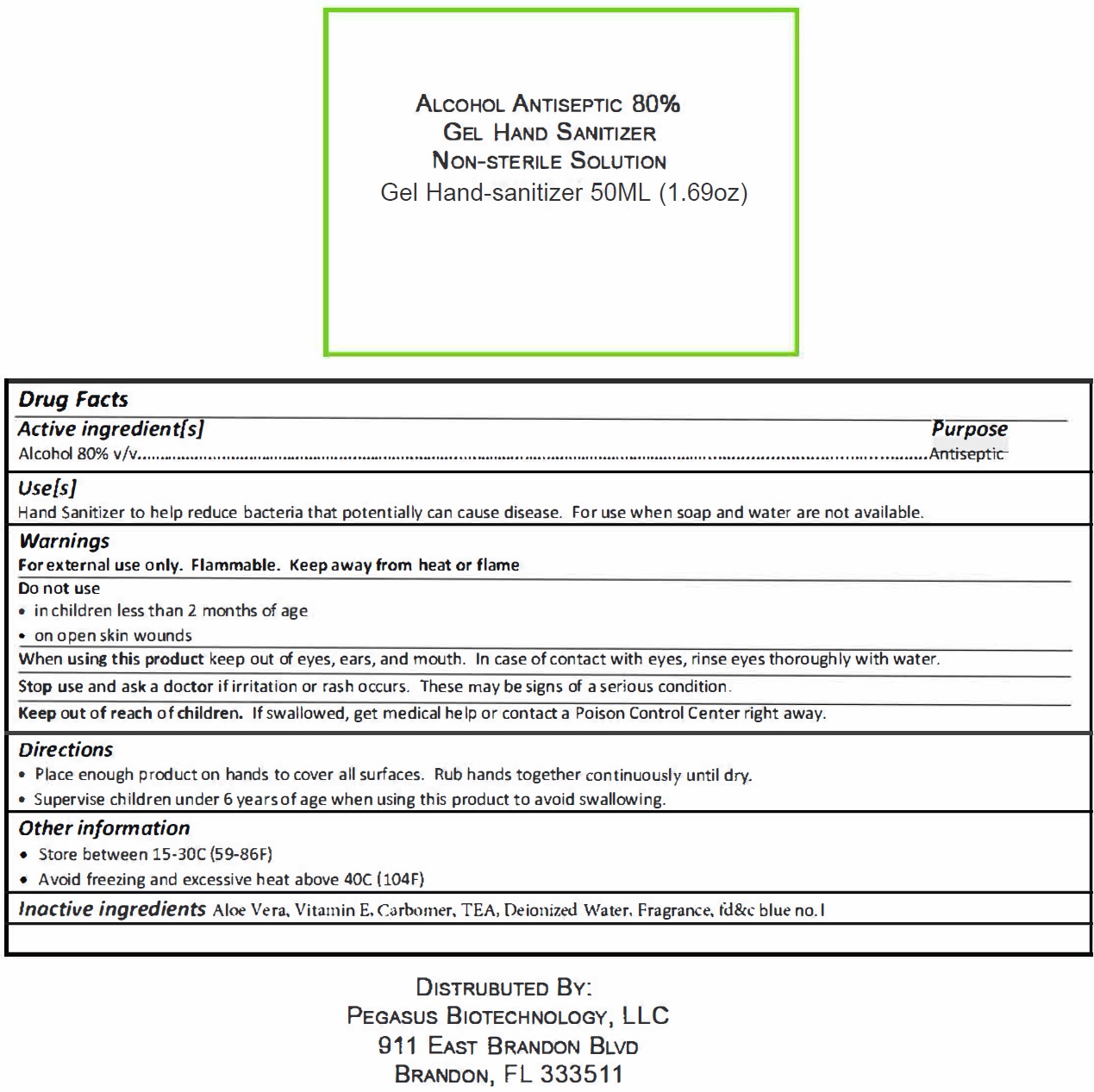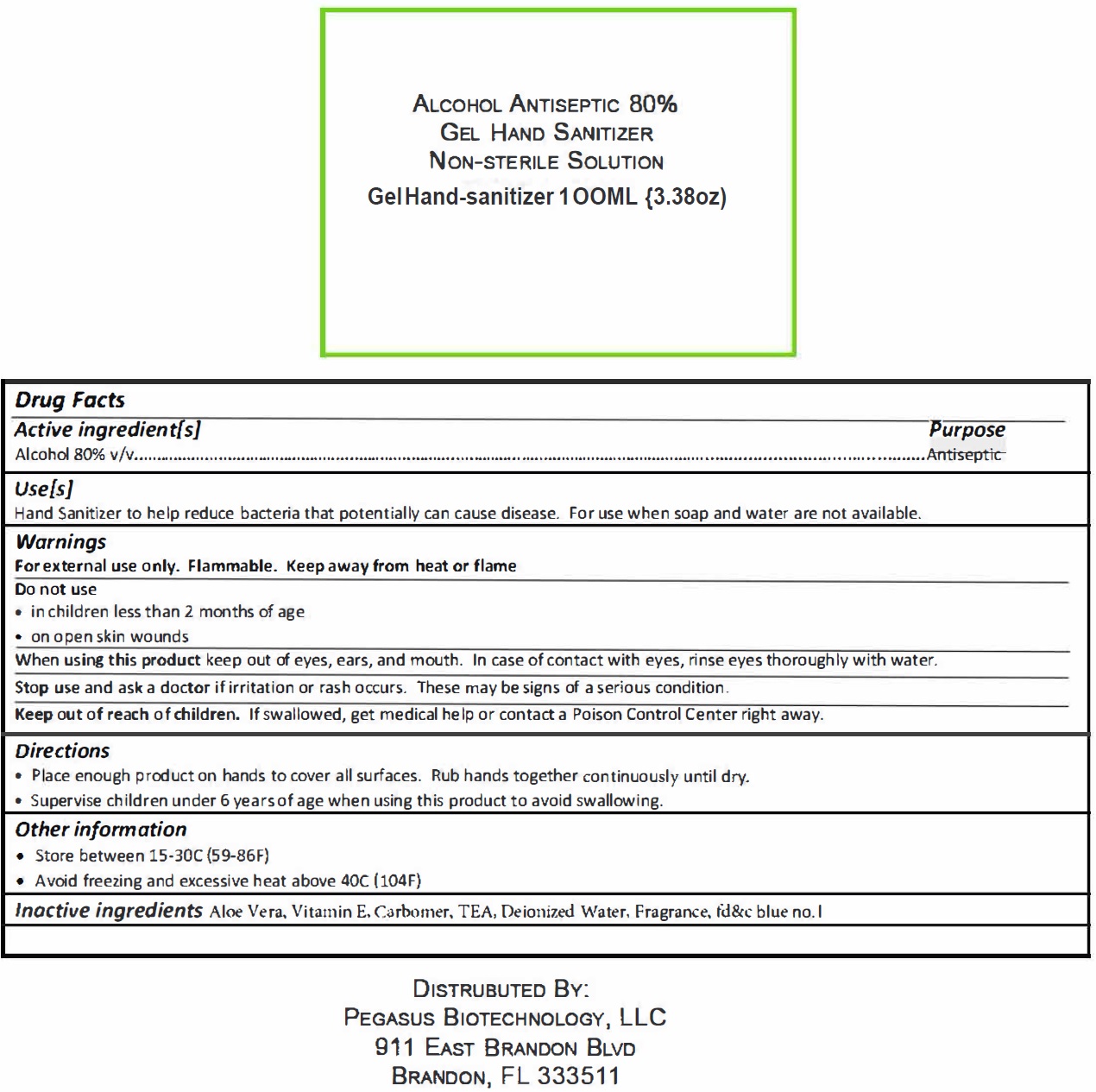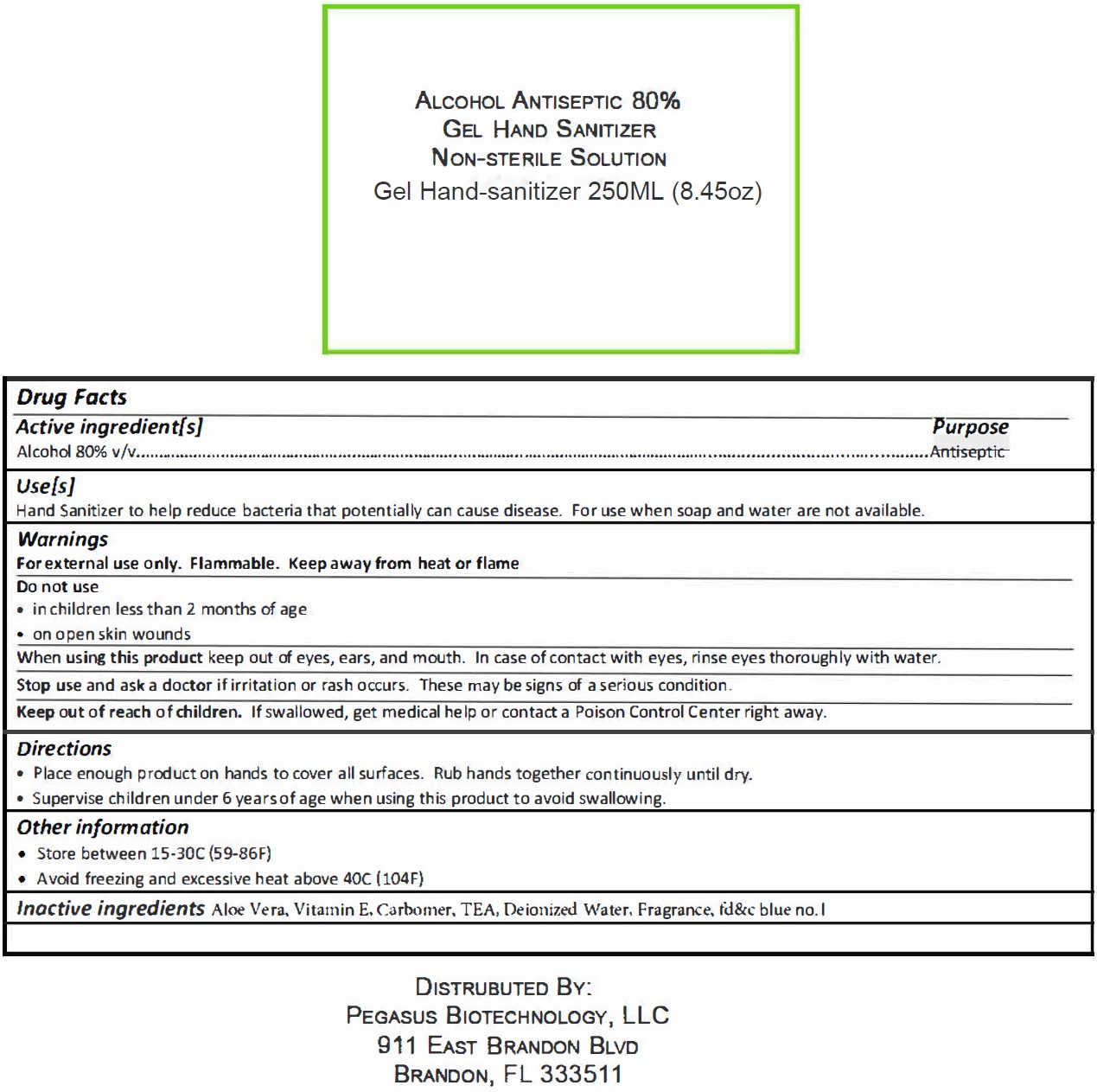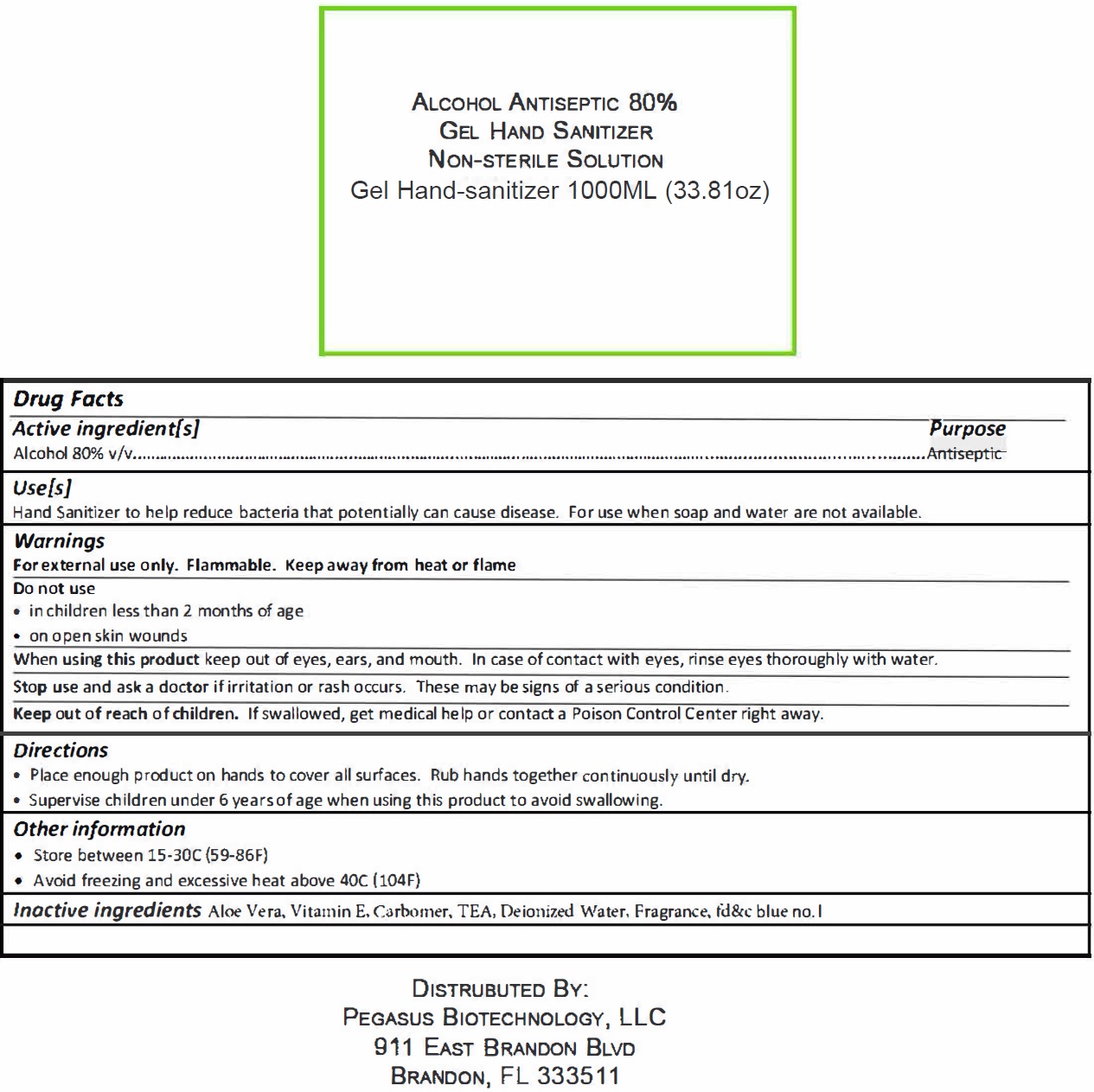 DRUG LABEL: Alcohol Antiseptic Hand Sanitizer Non-Sterile Solution
NDC: 80095-000 | Form: GEL
Manufacturer: Pegasus Biotechnology LLC.
Category: otc | Type: HUMAN OTC DRUG LABEL
Date: 20200901

ACTIVE INGREDIENTS: ALCOHOL 0.8 mL/1 mL
INACTIVE INGREDIENTS: ALOE VERA LEAF; .ALPHA.-TOCOPHEROL; CARBOMER HOMOPOLYMER, UNSPECIFIED TYPE; TEA LEAF; WATER; FD&C BLUE NO. 1

Alcohol Antiseptic Hand Sanitizer Non-Sterile Solution

Active ingredient[s]

Alcohol 80% v/v

Purpose

Antiseptic

Use[s]

Hand Sanitizer to help reduce bacteria that potentially can cause disease. For use when soap and water are not available.

Warnings

For external use only. Flammable. Keep away from heat or flame

Do not use

- in children less than 2 months of age
- on open skin wounds

When using this product

keep out of eyes, ears, and mouth. In case of contact with eyes, rinse eyes thoroughly with water.

Stop use and ask a doctor

if irritation or rash occurs. These may be signs of a serious condition.

Keep out of reach of chilren.

If swallowed, get medical help or contact a Poison Control Center

Directions

• Place enough product on hands to cover all surfaces. Rub hands together continuously until dry.
• Supervise children under 6 years of age when using this product to avoid swallowing.

Other information

• Store between 15-30C (59-86F)
• Avoid freezing and excessive heat above 40C (104F)

Inactive ingredients

Aloe Vera, Vitamin E, Carbomer, TEA, Deionized Water, Fragrance, fd&c blue no.1